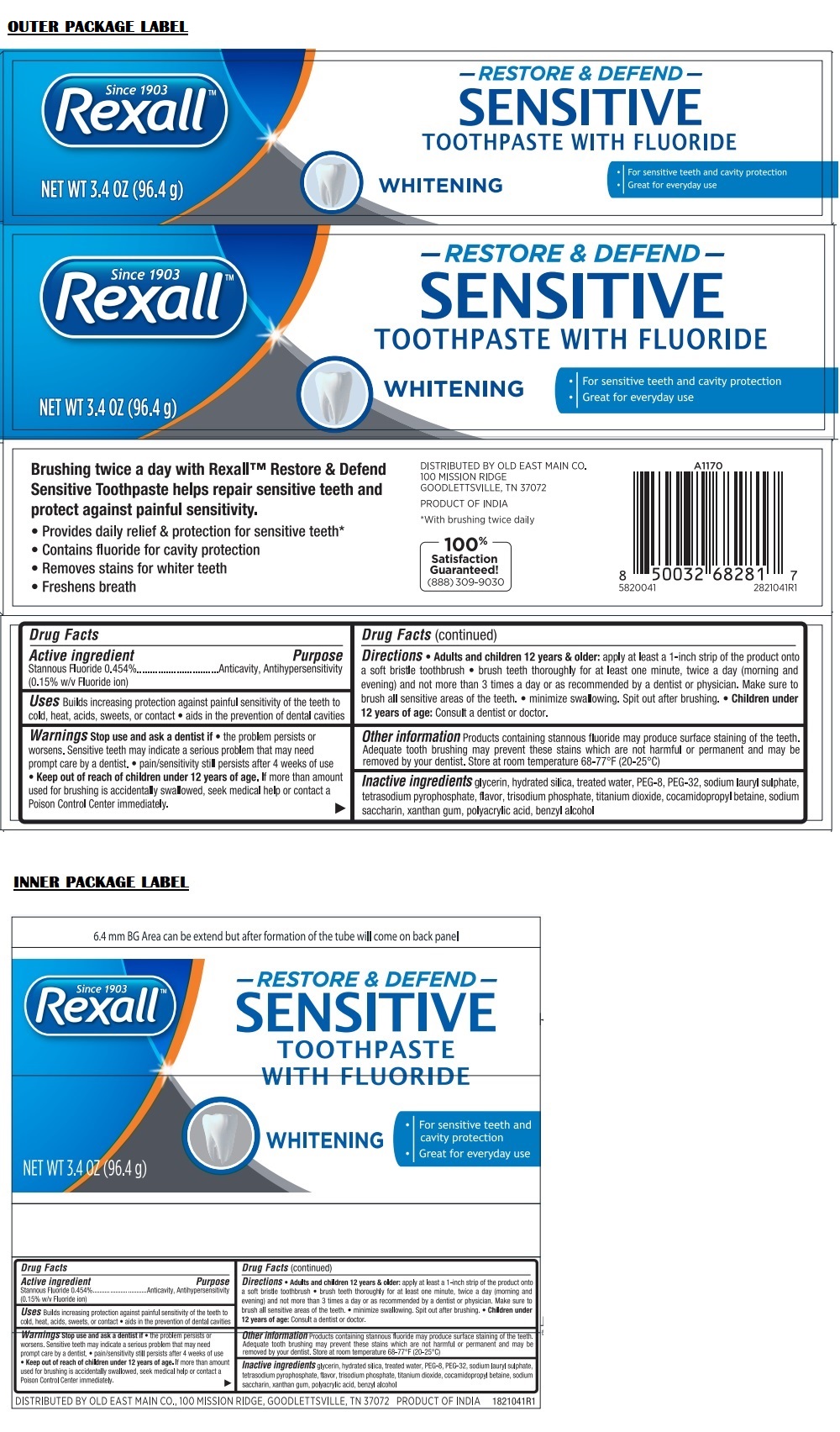 DRUG LABEL: Rexall Restore and Defend Sensitive Whitening
NDC: 55910-820 | Form: PASTE, DENTIFRICE
Manufacturer: Old East Main CO.
Category: otc | Type: HUMAN OTC DRUG LABEL
Date: 20241014

ACTIVE INGREDIENTS: STANNOUS FLUORIDE 4.54 mg/1 g
INACTIVE INGREDIENTS: GLYCERIN; SILICON DIOXIDE; WATER; POLYETHYLENE GLYCOL 400; POLYETHYLENE GLYCOL 1600; SODIUM LAURYL SULFATE; SODIUM PYROPHOSPHATE; SODIUM PHOSPHATE, TRIBASIC, DODECAHYDRATE; TITANIUM DIOXIDE; COCAMIDOPROPYL BETAINE; SACCHARIN SODIUM; XANTHAN GUM; CARBOMER HOMOPOLYMER TYPE B (ALLYL PENTAERYTHRITOL CROSSLINKED); BENZYL ALCOHOL

Rexall™ SENSITIVE TOOTHPASTE WITH FLUORIDE - WHITENING

Active ingredient

Stannous Fluoride 0.454%
(0.15% w/v Fluoride ion)

Purpose

Anticavity, Antihypersensitivity

Uses

Builds increasing protection against painful sensitivity of the teeth to cold, heat, acids, sweets, or contact • aids in the prevention of dental cavities

Warnings

Stop use and ask a dentist if • the problem persists or worsens. Sensitive teeth may indicate a serious problem that may need prompt care by a dentist. • pain/sensitivity still persists after 4 weeks of use

• Keep out of reach of children under 12 years of age. If more than amount used for brushing is accidentally swallowed, seek medical help or contact a Poison Control Center immediately.

Directions

• Adult and children 12 years & older: apply at least a 1-inch strip of the product onto a soft bristle toothbrush • brush teeth thoroughly for at least one minute, twice a day (morning and evening) and not more than 3 times a day or as recommended by a dentist or physician. Make sure to brush all sensitive areas of the teeth. • minimize swallowing. Spit out after brushing. • Children under 12 years of age: Consult a dentist or doctor.

Other information

Products containing stannous fluoride may produce surface staining of the teeth. Adequate tooth brushing may prevent these stains which are not harmful or permanent and may be removed by your dentist. Store at room temperature 68-77°F (20-25°C)

Inactive ingredients

glycerin, hydrated silica, treated water, PEG-8, PEG-32, sodium lauryl sulphate, tetrasodium pyrophosphate, flavor, trisodium phosphate, titanium dioxide, cocamidopropyl betaine, sodium saccharin, xanthan gum, polyacrylic acid, benzyl alcohol

Since 1903

TOOTHPASTE WITH FLUORIDE

• For sensitive teeth and cavity protection
• Great for everyday use

Brushing twice a day with Rexall™ Restore & Defend Sensitive Toothpaste helps repair sensitive teeth and protect against painful sensitivity.

• Provides daily relief & protection for sensitive teeth*
• Contains fluoride for cavity protection
• Removes stains for whiter teeth
• Freshens breath

100% Satisfaction Guaranteed!
(888) 309-9030

*With brushing twice daily

DISTRIBUTED BY OLD EAST MAIN CO.
100 MISSION RIDGE
GOODLETTSVILLE, TN 37072

PRODUCT OF INDIA